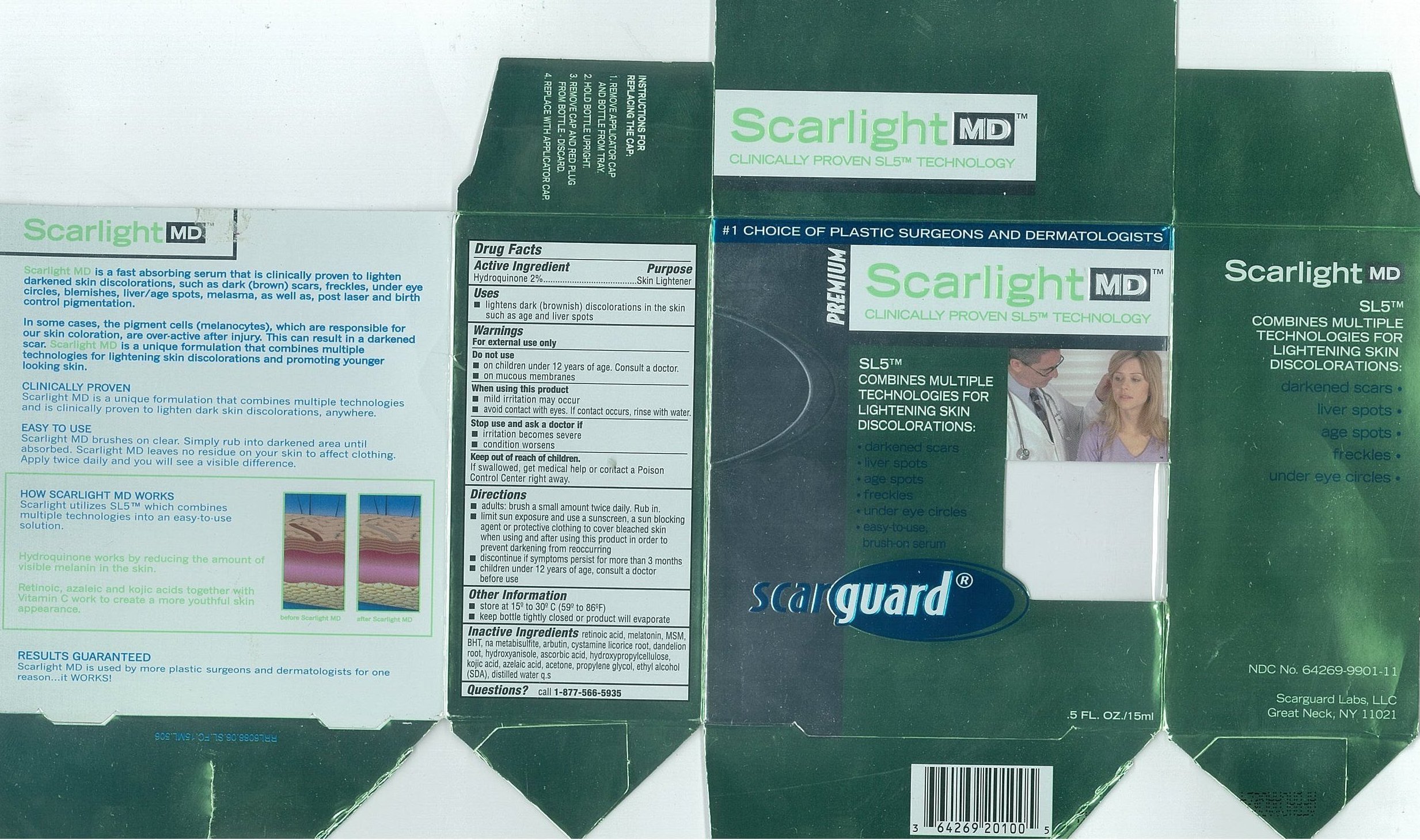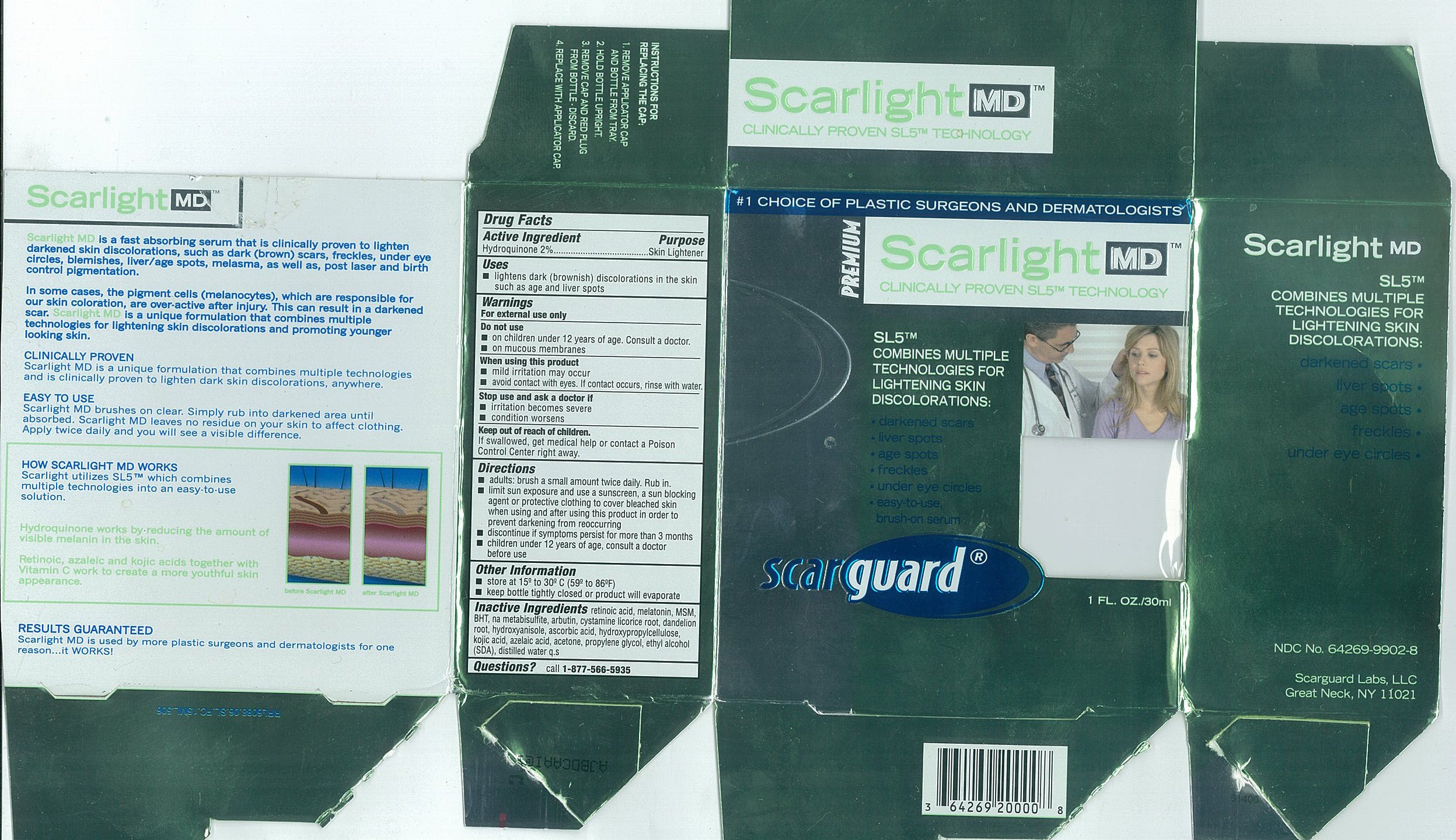 DRUG LABEL: Scarlight MD
NDC: 64269-9902 | Form: LIQUID
Manufacturer: Scarguard Labs, LLC
Category: otc | Type: HUMAN OTC DRUG LABEL
Date: 20091229

ACTIVE INGREDIENTS: HYDROQUINONE 20 mg/1 mL
INACTIVE INGREDIENTS: Propylene Glycol; Alcohol; Acetone; Azelaic Acid; Hydroxypropyl Cellulose; Ascorbic Acid; Butylated Hydroxyanisole; TARAXACUM OFFICINALE ROOT; Licorice; Arbutin; Sodium Metabisulfite; Butylated Hydroxytoluene; Dimethyl Sulfone; Melatonin; Tretinoin; Water; Kojic Acid; Cystamine

Drug Facts

Active Ingredients

Hydroquinone 2%

Purpose

Skin Lightener

Uses

- lightens dark (brownish) discoloration in the skin such as age and liver spots

Warnings

For external use only

Do not use

- on children under 12 years of age. Consult a doctor.
- on mucous membranes

When using this product

- mild irritation may occur
- avoid contact with eyes. If contact occurs, rinse with water.

Stop use and ask a doctor if

- irritation becomes severe
- condition worsens

Keep out of reach of children.

If swallowed, get medical help or contact a Poison Control Center right away.

Directions

- adults: brush a small amount twice daily. Rub in.
- limit sun exposure and use a sunscreen, a sun blocking agent or protective clothing to cover bleached skin when using and after using this product in order to prevent darkening from reoccurring
- discontinue if symptoms persist for more than 3 months
- children under 12 years of age, consult a doctor before use

Other Information

- store at 15º to 30ºC (59 to 86ºF)
- keep bottle tightly closed or product will evaporate

Inactive Ingredients

retinoic acid, melatonin, MSM, BHT, na metabisulfite, arbutin, cystamine, licorice root, dandelion root, hydroxyanisole, ascorbic acid, hydroxypropylcellulose, kojic acid, azelaic acid, acetone, propylene glycol, ethyl alcohol (SDA), distilled water q.s.

Questions

call

1-877-566-5935